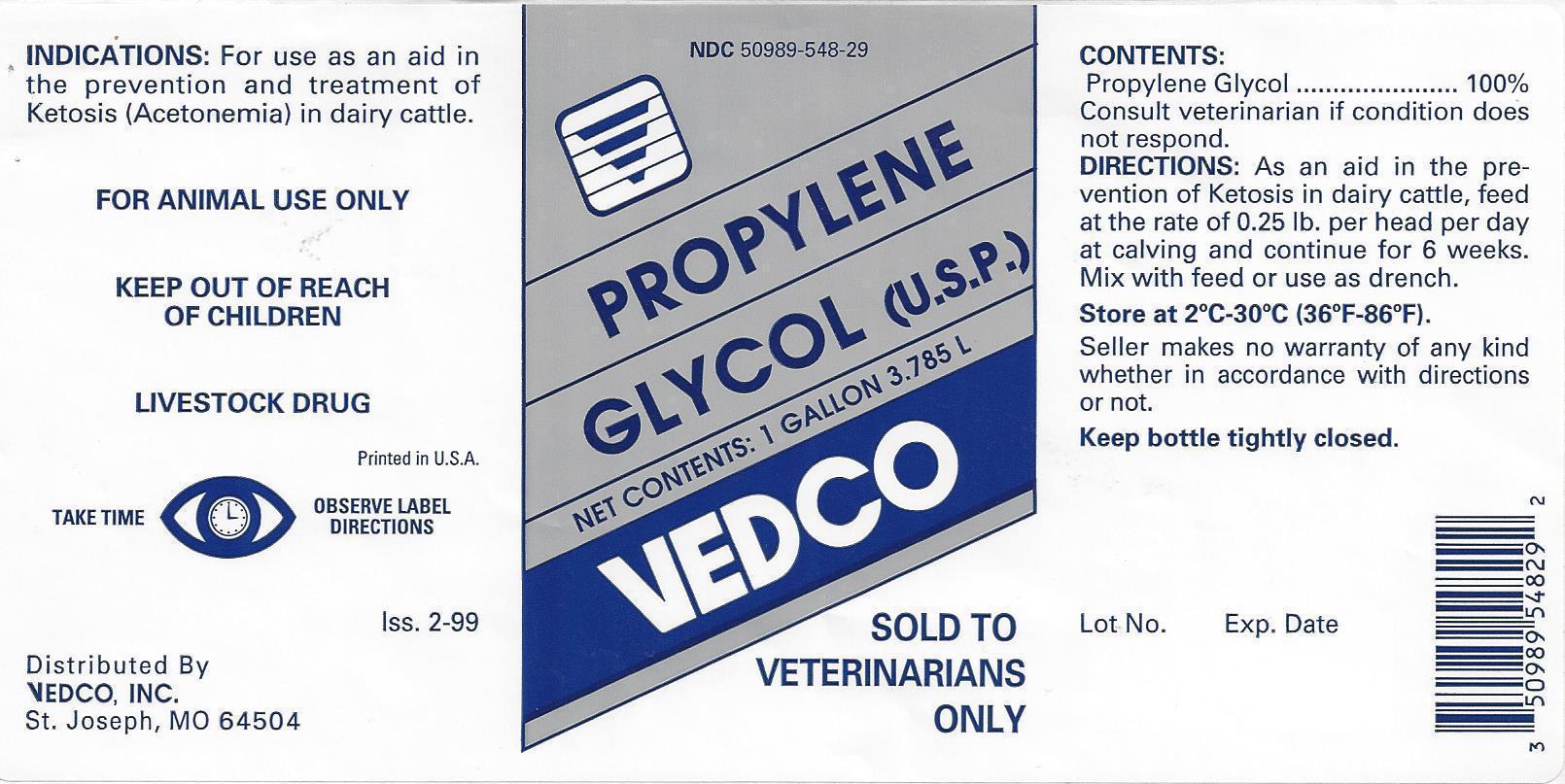 DRUG LABEL: PROPYLENE GLYCOL
NDC: 50989-548 | Form: LIQUID
Manufacturer: VEDCO
Category: animal | Type: OTC ANIMAL DRUG LABEL
Date: 20130903

ACTIVE INGREDIENTS: PROPYLENE GLYCOL 3.45 kg/3.45 kg

VEDCO PROPYLENE GLYCOL (U.S.P.)

NDC 50989-548-29 PROPYLENE GLYCOL (U.S.P.)

NET CONTENTS: 1 GALLON 3.785 L

VEDCO

SOLD TO VETERINARIANS ONLY

INDICATIONS:

For use as an aid in prevention and treatment of Ketosis (Acetonemia) in dairy cattle.

FOR ANIMAL USE ONLY

KEEP OUT OF REACH OF CHILDREN

LIVESTOCK DRUG

Printed in U.S.A.

TAKE TIME OBSERVE LABEL DIRECTIONS

Iss. 2-99

Distributed By

VEDCO, INC.

St. Joseph, MO 64504

CONTENTS:

Propylene Glycol............................100%

Consult veterinarian if condition does not respond.

DIRECTIONS:

As an aid in the prevention of Ketosis in dairy cattle, feed at the rate of 0.25 lb. per head per day at calving and continue for 6 weeks. Mix with feed or use as drench.

STORAGE AND HANDLING

Store at 2˚C - 30˚C (36˚F - 86˚F).

Seller makes no warranty of any kind whether in accordance with directions or not.

Keep bottle tightly closed.

Lot No. Exp. Date